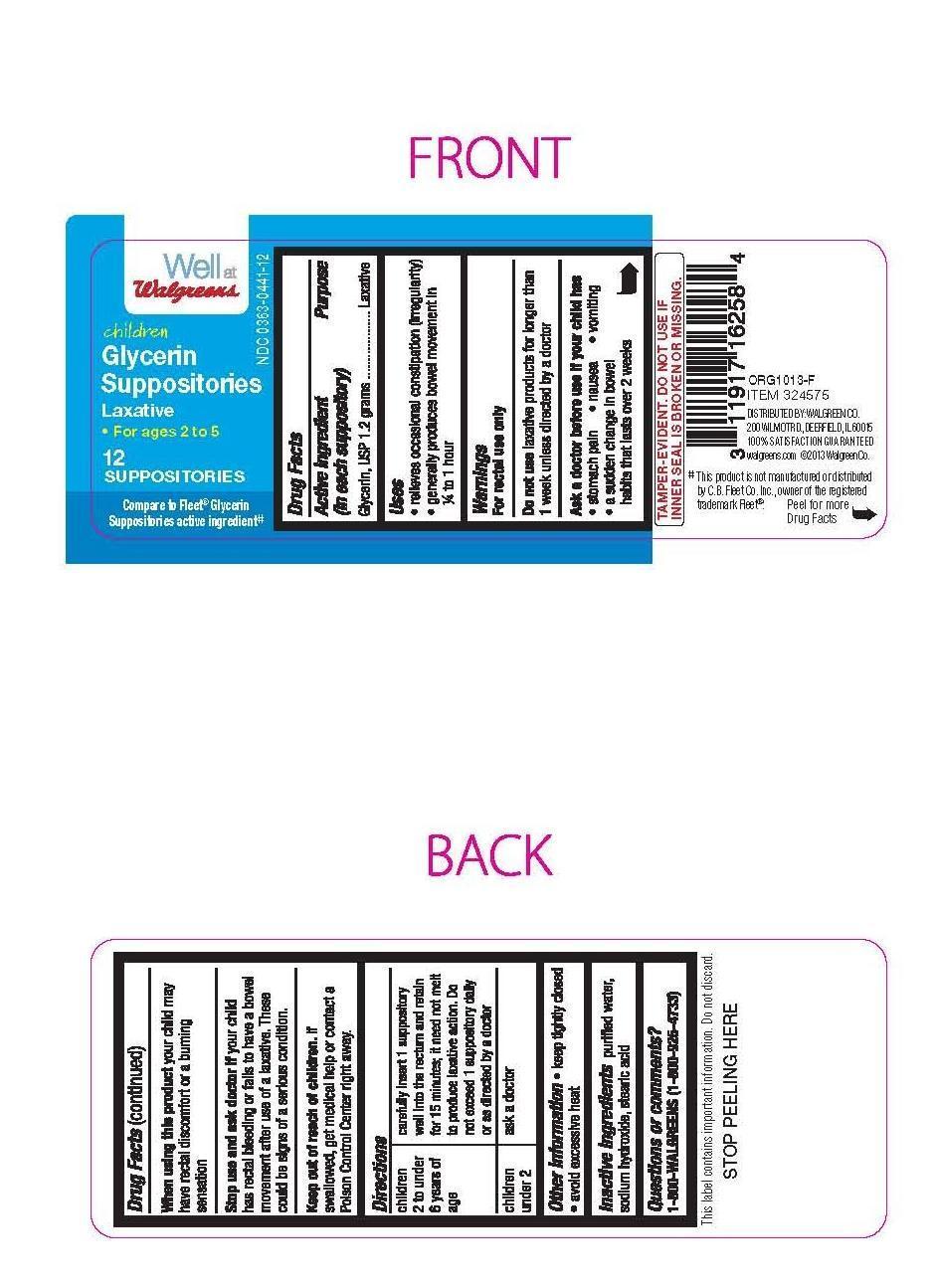 DRUG LABEL: Walgreens Children Glycerin
NDC: 0363-0440 | Form: SUPPOSITORY
Manufacturer: Walgreens
Category: otc | Type: HUMAN OTC DRUG LABEL
Date: 20141006

ACTIVE INGREDIENTS: GLYCERIN 83 g/100 g
INACTIVE INGREDIENTS: STEARIC ACID 8.5 g/100 g; SODIUM HYDROXIDE 1.2 g/100 g; WATER 7.3 g/100 g

Active Ingredient

Active Ingredient Purpose
(in each suppository)
Glycerin, USP 1.2 g........................................................Laxative

Uses

-relieves occasional constipation (irregularity)

-generally produces bowel movement in 1/4 to 1 hour

Warnings

For rectal use only

Ask a doctor before use if your child has

- stomach pain -nausea -vomiting

- a sudden change in bowel habits lasting more than 2 weeks

Stop use and ask a doctor if your child has rectal bleeding or fails to have a bowel movement after use of a laxative.

These could be signs of a serious condition.

Keep out of reach of children.

If swallowed, get medical help or contact a Poison Control Center right away.

Directions

children 2 to under 6 years 1 suppository, or as directed by doctor

children under 2 years ask a doctor

Insert suppository well up into rectum.

Suppository need not melt completely to produce laxative action.

Other information

-keep tightly closed.

-avoid excessive heat.

Inactive ingredients

purified water, sodium hydroxide, stearic acid

Directions

children 2 to under 6 years of age carefully insert 1 suppository well into the rectum and retain for 15 minutes; it need not melt to produce laxative action. Do not exceed 1 suppository daily or as directed by a doctor.

children under 2 ask a doctor

Do not use laxative products for longer than 1 week unless directed by a doctor

When using this product your child may have rectal discomfort or a burning sensation.